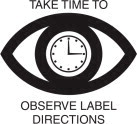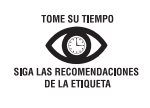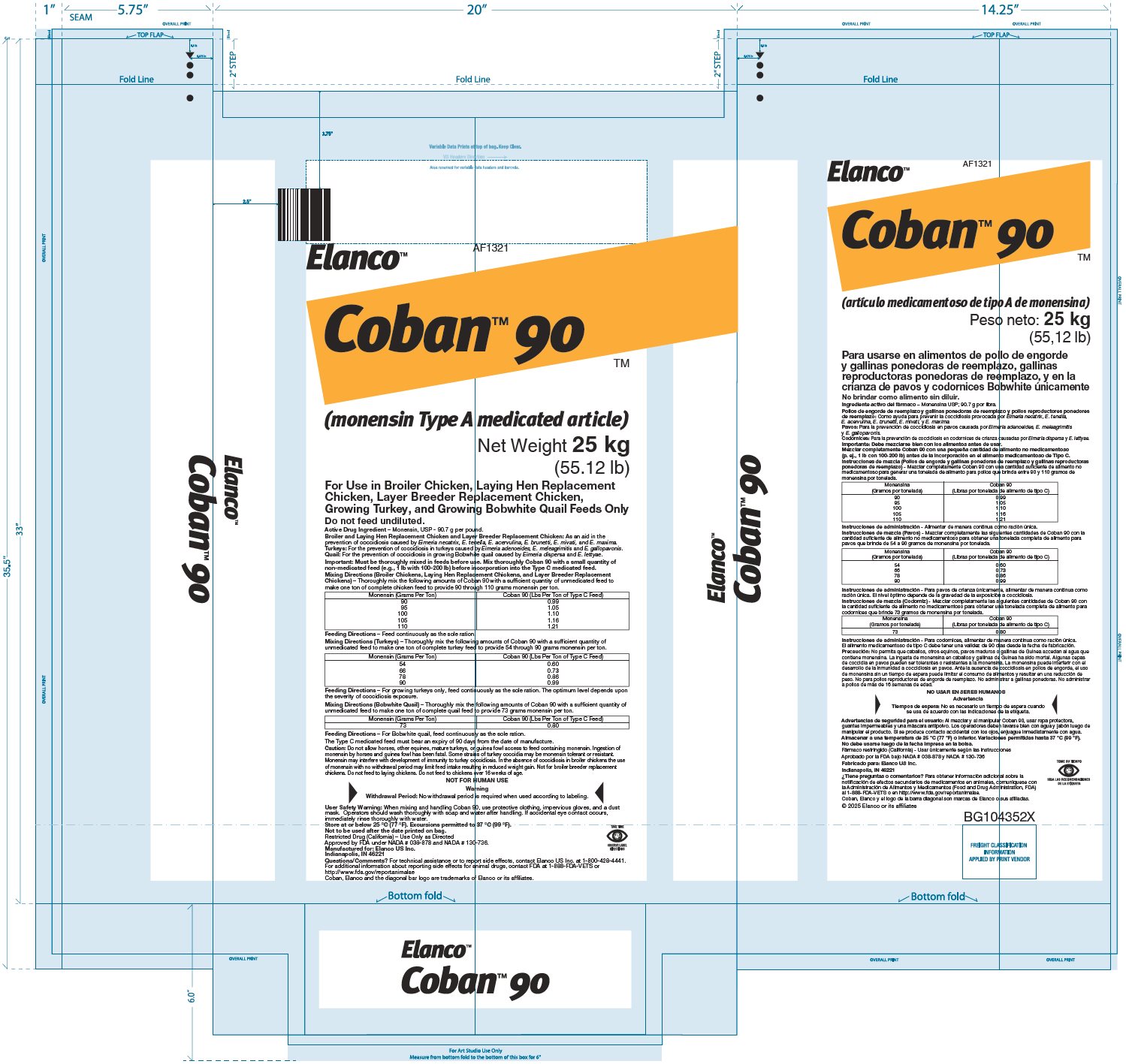 DRUG LABEL: Coban 90
NDC: 58198-1321 | Form: GRANULE
Manufacturer: Elanco US Inc.
Category: animal | Type: OTC TYPE A MEDICATED ARTICLE ANIMAL DRUG LABEL
Date: 20250807

ACTIVE INGREDIENTS: monensin 200 g/1 kg

Elanco™

AF1321

Coban™ 90 TM

(monensin Type A medicated article)

Net Weight 25 kg
(55.12 lb)

For Use in Broiler Chicken, Laying Hen Replacement Chicken, Layer Breeder Replacement Chicken, Growing Turkey, and Growing Bobwhite Quail Feeds Only

Do not feed undiluted.

ACTIVE INGREDIENT

Active Drug Ingredient – Monensin, USP - 90.7 g per pound.

Broiler and Laying Hen Replacement Chicken and Layer Breeder Replacement Chicken: As an aid in the prevention of coccidiosis caused by Eimeria necatrix, E. tenella, E. acervulina, E. brunetti, E. mivati, and E. maxima.

Turkeys: For the prevention of coccidiosis in turkeys caused by Eimeria adenoeides, E. meleagrimitis and E. gallopavonis.

Quail: For the prevention of coccidiosis in growing Bobwhite quail caused by Eimeria dispersa and E. lettyae.

Important: Must be thoroughly mixed in feeds before use. Mix thoroughly Coban 90 with a small quantity of non-medicated feed (e.g., 1 lb with 100-200 lb) before incorporation into the Type C medicated feed.

DOSAGE AND ADMINISTRATION

Mixing Directions (Broiler Chickens, Laying Hen Replacement Chickens, and Layer Breeder Replacement Chickens) – Thoroughly mix the following amounts of Coban 90 with a sufficient quantity of unmedicated feed to make one ton of complete chicken feed to provide 90 through 110 grams monensin per ton.

Monensin (Grams Per Ton) | Coban 90 (Lbs Per Ton of Type C Feed)
90 | 0.99
95 | 1.05
100 | 1.10
105 | 1.16
110 | 1.21

Feeding Directions – Feed continuously as the sole ration.

DOSAGE AND ADMINISTRATION

Mixing Directions (Turkeys) – Thoroughly mix the following amounts of Coban 90 with a sufficient quantity of unmedicated feed to make one ton of complete turkey feed to provide 54 through 90 grams monensin per ton.

Monensin (Grams Per Ton) | Coban 90 (Lbs Per Ton of Type C Feed)
54 | 0.60
66 | 0.73
78 | 0.86
90 | 0.99

Feeding Directions – For growing turkeys only, feed continuously as the sole ration. The optimum level depends upon the severity of coccidiosis exposure.

DOSAGE AND ADMINISTRATION

Mixing Directions (Bobwhite Quail) – Thoroughly mix the following amounts of Coban 90 with a sufficient quantity of unmedicated feed to make one ton of complete quail feed to provide 73 grams monensin per ton.

Monensin (Grams Per Ton) | Coban 90 (Lbs Per Ton of Type C Feed)
73 | 0.80

Feeding Directions – For Bobwhite quail, feed continuously as the sole ration.

The Type C medicated feed must bear an expiry of 90 days from the date of manufacture.

Caution: Do not allow horses, other equines, mature turkeys, or guinea fowl access to feed containing monensin. Ingestion of monensin by horses and guinea fowl has been fatal. Some strains of turkey coccidia may be monensin tolerant or resistant. Monensin may interfere with development of immunity to turkey coccidiosis. In the absence of coccidiosis in broiler chickens the use of monensin with no withdrawal period may limit feed intake resulting in reduced weight gain. Not for broiler breeder replacement chickens. Do not feed to laying chickens. Do not feed to chickens over 16 weeks of age.

WARNINGS

NOT FOR HUMAN USE

Warning

Withdrawal Period: No withdrawal period is required when used according to labeling.

User Safety Warning: When mixing and handling Coban 90, use protective clothing, impervious gloves, and a dust mask. Operators should wash thoroughly with soap and water after handling. If accidental eye contact occurs, immediately rinse thoroughly with water.

STORAGE AND HANDLING

Store at or below 25 °C (77 °F). Excursions permitted to 37 °C (99 °F).

Not to be used after the date printed on bag.

Restricted Drug (California) – Use Only as Directed

Approved by FDA under NADA # 038-878 and NADA # 130-736.

Manufactured for: Elanco US Inc.

Indianapolis, IN 46221

Questions/Comments? For technical assistance or to report side effects, contact Elanco US Inc. at 1-800-428-4441.

For additional information about reporting side effects for animal drugs, contact FDA at 1-888-FDA-VETS or http://www.fda.gov/reportanimalae

Coban, Elanco and the diagonal bar logo are trademarks of Elanco or its affiliates.

Elanco™

AF1321

Coban™ 90 TM

(artículo medicamentoso de tipo A de monensina)

Peso neto: 25 kg
(55,12 lb)

Para usarse en alimentos de pollo de engorde y gallinas ponedoras de reemplazo, gallinas reproductoras ponedoras de reemplazo, y en la crianza de pavos y codornices Bobwhite únicamente

No brindar como alimento sin diluir.

ACTIVE INGREDIENT

Ingrediente activo del fármaco – Monensina USP; 90.7 g por libra.

INDICATIONS AND USAGE

Pollos de engorde de reemplazo y gallinas ponedoras de reemplazo y pollos reproductores ponedores de reemplazo: Como ayuda para prevenir la coccidiosis provocada por Eimeria necatrix, E. tenella, E. acervulina, E. brunetti, E. mivati, y E. maxima.

Pavos: Para la prevención de coccidiosis en pavos causada por Eimeria adenoeides, E. meleagrimitis y E. gallopavonis.

Codornices: Para la prevención de coccidiosis en codornices de crianza causadas por Eimeria dispersa y E. lettyae.

Importante: Debe mezclarse bien con los alimentos antes de usar.

Mezclar completamente Coban 90 con una pequeña cantidad de alimento no medicamentoso (p. ej., 1 lb con 100-200 lb) antes de la incorporación en el alimento medicamentoso de Tipo C.

Instrucciones de mezcla (Pollos de engorde y gallinas ponedoras de reemplazo y gallinas reproductoras ponedoras de reemplazo) - Mezclar completamente Coban 90 con una cantidad suficiente de alimento no medicamentoso para generar una tonelada de alimento para pollos que brinda entre 90 y 110 gramos de monensina por tonelada.

Monensina (Gramos por tonelada) | Coban 90 (Libras por tonelada de alimento de tipo C)
90 | 0.99
95 | 1.05
100 | 1.10
105 | 1.16
110 | 1.21

Instrucciones de administración - Alimentar de manera continua como ración única.

Instrucciones de mezcla (Pavos) - Mezclar completamente las siguientes cantidades de Coban 90 con la cantidad suficiente de alimento no medicamentoso para obtener una tonelada completa de alimento para pavos que brinde de 54 a 90 gramos de monensina por tonelada.

Monensina (Gramos por tonelada) | Coban 90 (Libras por tonelada de alimento de tipo C)
54 | 0.60
66 | 0.73
78 | 0.86
90 | 0.99

Instrucciones de administración - Para pavos de crianza únicamente, alimentar de manera continua como ración única. El nivel óptimo depende de la gravedad de la exposición a coccidiosis.

Instrucciones de mezcla (Codorniz) - Mezclar completamente las siguientes cantidades de Coban 90 con la cantidad suficiente de alimento no medicamentoso para obtener una tonelada completa de alimento para codornices que brinde 73 gramos de monensina por tonelada.

Monensina (Gramos por tonelada) | Coban 90 (Libras por tonelada de alimento de tipo C)
73 | 0.80

Instrucciones de administración - Para codornices, alimentar de manera continua como ración única.

El alimento medicamentoso de tipo C debe tener una validez de 90 días desde la fecha de fabricación.

Precaución: No permita que caballos, otros equinos, pavos maduros o gallinas de Guinea accedan al agua que contiene monensina. La ingesta de monensina en caballos y gallinas de Guinea ha sido mortal. Algunas cepas de coccidia en pavos pueden ser tolerantes o resistentes a la monensina. La monensina puede interferir con el desarrollo de la inmunidad a coccidiosis en pavos. Ante la ausencia de coccidiosis en pollos de engorde, el uso de monensina sin un tiempo de espera puede limitar el consumo de alimentos y resultar en una reducción de peso. No para pollos reproductores de engorde de reemplazo. No administrar a gallinas ponedoras. No administrar a pollos de más de 16 semanas de edad.

WARNINGS

NO USAR EN SERES HUMANOS

Advertencia

Tiempos de espera: No es necesario un tiempo de espera cuando se usa de acuerdo con las indicaciones de la etiqueta.

Advertencias de seguridad para el usuario: Al mezclar y al manipular Coban 90, usar ropa protectora, guantes impermeables y una máscara antipolvo. Los operadores deben lavarse bien con agua y jabón luego de manipular el producto. Si se produce contacto accidental con los ojos, enjuague inmediatamente con agua.

Almacenar a una temperatura de 25 °C (77 °F) o inferior. Variaciones permitidas hasta 37 °C (99 °F).

No debe usarse luego de la fecha impresa en la bolsa.

Fármaco restringido (California) - Usar únicamente según las instrucciones

Aprobado por la FDA bajo NADA # 038-878 y NADA # 130-736

Fabricado para: Elanco US Inc.

Indianapolis, IN 46221

¿Tiene preguntas o comentarios? Para obtener información adicional sobre la notificación de efectos secundarios de medicamentos en animales, comuníquese con la Administración de Alimentos y Medicamentos (Food and Drug Administration, FDA) al 1-888-FDA-VETS o en http://www.fda.gov/reportanimalae.

Coban, Elanco y el logo de la barra diagonal son marcas de Elanco o sus afiliadas.

© 2025 Elanco or its affiliates

BG104352X

Principal Display Panel - 200 g/kg Bag Label

Elanco™ AF1321

Coban™ 90 TM

(monensin Type A medicated article)

Net Weight 25 kg

(55.12 lb)